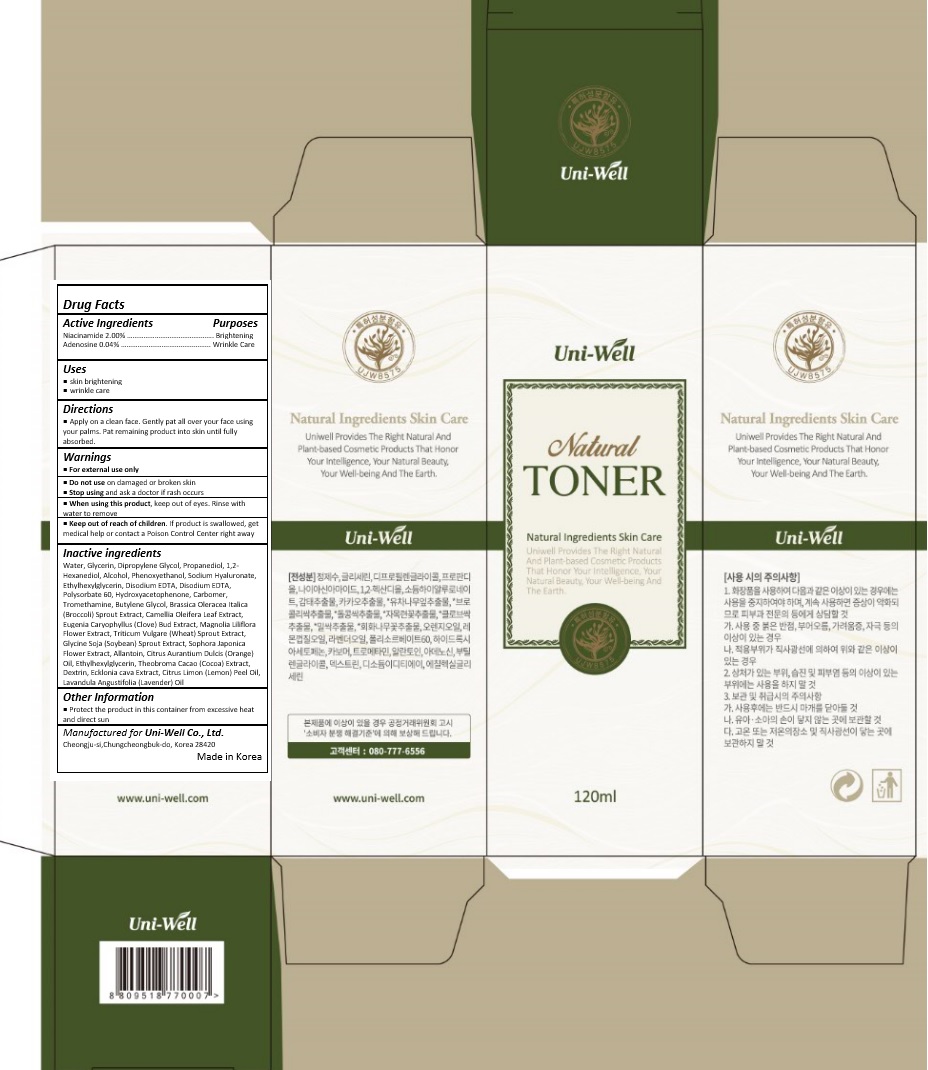 DRUG LABEL: UNIWELL NATURAL TONER
NDC: 71502-004 | Form: LIQUID
Manufacturer: uniwell LTD
Category: otc | Type: HUMAN OTC DRUG LABEL
Date: 20170614

ACTIVE INGREDIENTS: NIACINAMIDE 2.4 mg/120 mL; ADENOSINE 0.048 mg/120 mL
INACTIVE INGREDIENTS: WATER; GLYCERIN; PROPANEDIOL; DIPROPYLENE GLYCOL; 1,2-HEXANEDIOL; ALCOHOL; PHENOXYETHANOL; HYALURONATE SODIUM; ETHYLHEXYLGLYCERIN; EDETATE DISODIUM ANHYDROUS; POLYSORBATE 60; TROMETHAMINE; BUTYLENE GLYCOL; BROCCOLI SPROUT; CAMELLIA OLEIFERA LEAF; CLOVE; MAGNOLIA LILIIFLORA FLOWER; WHEAT SPROUT; SOYBEAN; STYPHNOLOBIUM JAPONICUM FLOWER; ALLANTOIN; ORANGE OIL; COCOA; LEMON OIL; LAVENDER OIL

Drug Facts

ACTIVE INGREDIENT

NIACINAMIDE 2.00%

ADENOSINE 0.04%

PURPOSE

Brighting and Wrinkle Care

INDICATIONS AND USAGE

skin brightening
wrinkle care

DOSAGE AND ADMINISTRATION

Apply on a clean face. Gently pat all over your face using your palms. Pat remaining product into skin until fully absorbed.

WARNINGS

For external use only.
Do not use on damaged or broken skin.
When using this product, keep out of eyes. Rinse with water to remove.
Stop using and ask a doctor if rash occurs.

KEEP OUT OF REACH OF CHILDREN

Keep out of reach of the children. If product is swallowed, get medical help or contact a poison control center right away.

INACTIVE INGREDIENT

Water, Glycerin, Dipropylene Glycol, Propanediol, 1,2-Hexanediol, Alcohol, Phenoxyethanol, Sodium Hyaluronate, Ethylhexylglycerin, Disodium EDTA, Disodium EDTA, Polysorbate 60, Hydroxyacetophenone, Carbomer, Tromethamine, Butylene Glycol, Brassica Oleracea Italica (Broccoli) Sprout Extract, Camellia Oleifera Leaf Extract, Eugenia Caryophyllus (Clove) Bud Extract, Magnolia Liliflora Flower Extract, Triticum Vulgare (Wheat) Sprout Extract, Glycine Soja (Soybean) Sprout Extract, Sophora Japonica Flower Extract, Allantoin, Citrus Aurantium Dulcis (Orange) Oil, Ethylhexylglycerin, Theobroma Cacao (Cocoa) Extract, Dextrin, Ecklonia cava Extract, Citrus Limon (Lemon) Peel Oil, Lavandula Angustifolia (Lavender) Oil